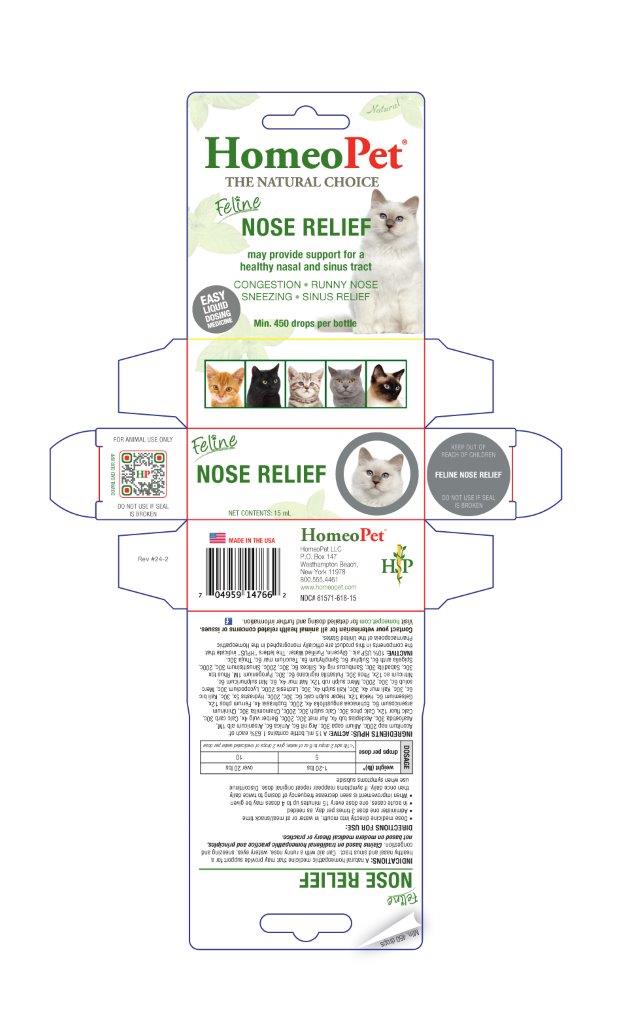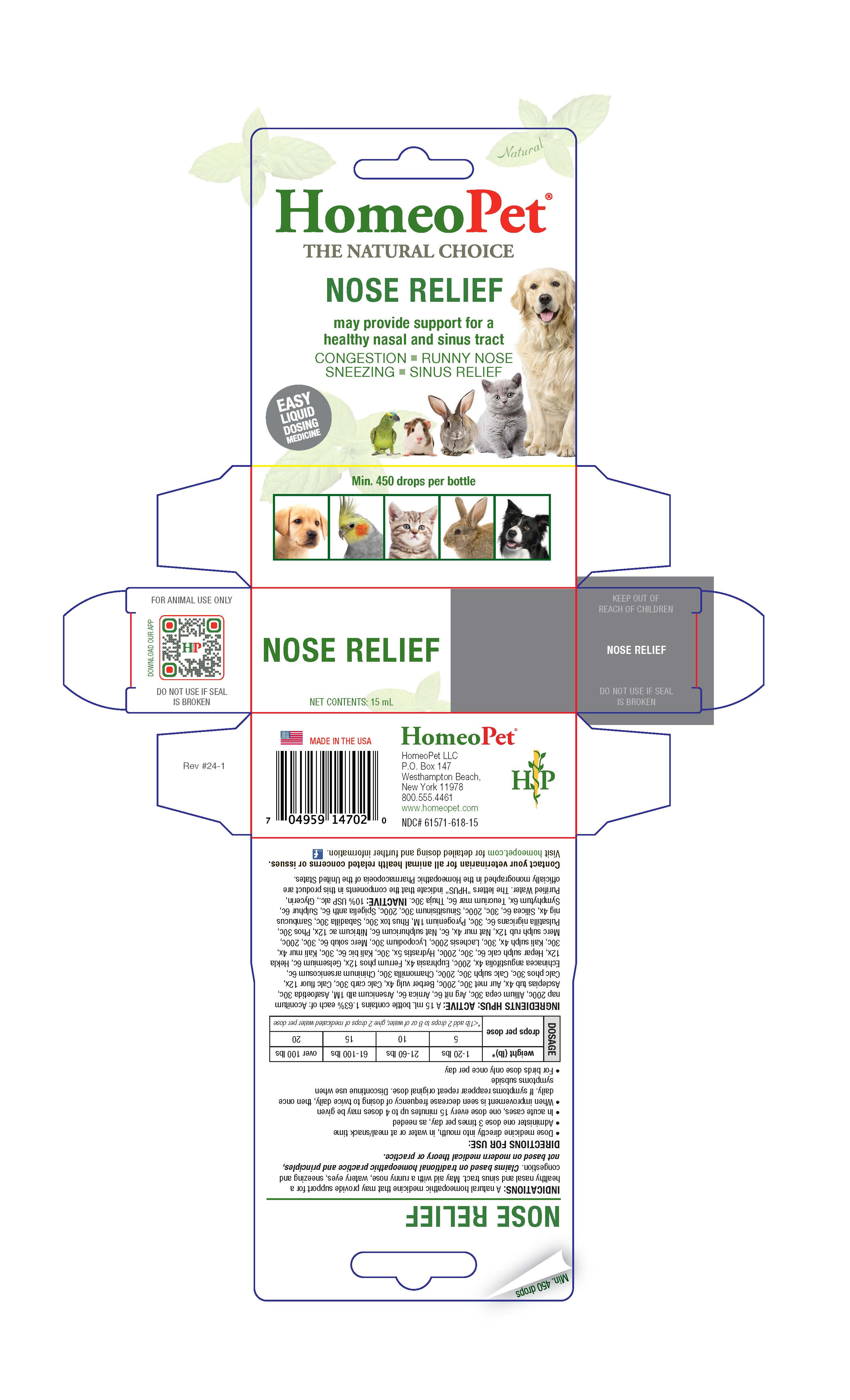 DRUG LABEL: Nose Relief
NDC: 61571-618 | Form: LIQUID
Manufacturer: HomeoPet, LLC
Category: homeopathic | Type: OTC ANIMAL DRUG LABEL
Date: 20241121

ACTIVE INGREDIENTS: ACONITUM NAPELLUS 200 [hp_C]/15 mL; ONION 30 [hp_C]/15 mL; SILVER NITRATE 6 [hp_C]/15 mL; ARNICA MONTANA 6 [hp_C]/15 mL; ARSENIC TRIOXIDE 1 [hp_M]/15 mL; FERULA ASSA-FOETIDA RESIN 30 [hp_C]/15 mL; ASCLEPIAS TUBEROSA ROOT 4 [hp_X]/15 mL; GOLD 30 [hp_C]/15 mL; BERBERIS VULGARIS ROOT BARK 4 [hp_X]/15 mL; OYSTER SHELL CALCIUM CARBONATE, CRUDE 30 [hp_C]/15 mL; CALCIUM FLUORIDE 12 [hp_X]/15 mL; TRIBASIC CALCIUM PHOSPHATE 30 [hp_C]/15 mL; CALCIUM SULFATE ANHYDROUS 30 [hp_C]/15 mL; MATRICARIA CHAMOMILLA 30 [hp_C]/15 mL; QUININE ARSENITE 6 [hp_C]/15 mL; ECHINACEA ANGUSTIFOLIA 4 [hp_X]/15 mL; EUPHRASIA STRICTA 4 [hp_X]/15 mL; FERROSOFERRIC PHOSPHATE 12 [hp_X]/15 mL; GELSEMIUM SEMPERVIRENS ROOT 6 [hp_C]/15 mL; HEKLA LAVA 12 [hp_X]/15 mL; CALCIUM SULFIDE 6 [hp_C]/15 mL; GOLDENSEAL 5 [hp_X]/15 mL; POTASSIUM DICHROMATE 6 [hp_C]/15 mL; POTASSIUM CHLORIDE 4 [hp_X]/15 mL; POTASSIUM SULFATE 4 [hp_X]/15 mL; LACHESIS MUTA VENOM 200 [hp_C]/15 mL; LYCOPODIUM CLAVATUM SPORE 30 [hp_C]/15 mL; MERCURIUS SOLUBILIS 6 [hp_C]/15 mL; MERCURIC SULFIDE 12 [hp_X]/15 mL; SODIUM CHLORIDE 4 [hp_X]/15 mL; SODIUM SULFATE 6 [hp_C]/15 mL; NITRIC ACID 12 [hp_X]/15 mL; PHOSPHORUS 30 [hp_C]/15 mL; ANEMONE PRATENSIS 6 [hp_C]/15 mL; RANCID BEEF 1 [hp_M]/15 mL; TOXICODENDRON PUBESCENS LEAF 30 [hp_C]/15 mL; SCHOENOCAULON OFFICINALE SEED 30 [hp_C]/15 mL; SAMBUCUS NIGRA FLOWERING TOP 4 [hp_X]/15 mL; SILICON DIOXIDE 6 [hp_C]/15 mL; SINUSITISINUM 30 [hp_C]/15 mL; SPIGELIA ANTHELMIA 6 [hp_C]/15 mL; SULFUR 6 [hp_C]/15 mL; COMFREY ROOT 6 [hp_X]/15 mL; TEUCRIUM MARUM 6 [hp_C]/15 mL; THUJA OCCIDENTALIS LEAFY TWIG 30 [hp_C]/15 mL
INACTIVE INGREDIENTS: ALCOHOL; WATER; GLYCERIN

Nose Relief

Nose ReliefFeline Nose Relief

May provide support for a healthy nasal and sinus tract

CONGESTION - RUNNY NOSE - SNEEZING - SINUS RELIEF

Directions for Use and Dosage

- Dose remedy directly into mouth, in water or at meal/snack time
- Administer one dose 3 times per day, as needed
- In acute cases, one dose every 15 minutes up to 4 doses may be given
- When improvement is seen decrease frequency of dosing to twice daily, then once daily. If symptoms reappear repeat original dose. Discontinue use when symptoms subside
- For birds dose only once per day

Multispecies Dosing

Dosage | weight (lb)* | 1-20 lbs | 21-60 lbs | 61-100 lbs | over 100 lbs
Dosage | drops per dose | 5 | 10 | 15 | 20
Dosage | drops per dose | *<1 lb add 2 drops to 8 oz of water, give 2 drops of medicated water per dose

Feline Dosing

Dosage | weight (lb)* | 1-20 lbs | over 20 lbs
Dosage | drops per dose | 5 | 10
Dosage | drops per dose | *<1 lb add 2 drops to 8 oz of water, give 2 drops of medicated water per dose

Contact Veterinarian

Contact your veterinarian for all animal health related cocerns or issues.

Visit homeopet.com for detailed dosing and further information.

Ingredients HPUS: ACTIVE

Aconitum nap 200c, Allium cepa 30c, Arg nit 6c, Arnica 6c, Arsenicum alb 1M, Asafoetida 30c, Asclepias tub 4x, Aur met 30c, 200c, Berber vulg 4x, Calc carb 30c, Calc flour 12x, Calc phos 30c, Calc sulph 30c, 200c, Chamomilla 30c, Chininum arsenicosum 6c, Echinacea angustifolia 4x, 200c, Euphrasia 4x, Ferrum phos 12x, Gelsemium 6c, Hekla 12x, Hepar sulph calc 6c, 30c, 200c, Hydrastis 5x, 30c, Kali bic 6c, 30c, Kali mur 4x, 30c, Kali sulph 4x, 30c, Lachesis 200c, Lycopodium 30c, Merc solub 6c, 30c, 200c, Merc sulph rub 12x, Nat mur 4x, 6c, Nat sulphuricum 6c, Nitricum ac 12x, Phos 30c, Pulsatilla nigricans 6c, 30c, Pyrogenium 1M, Rhus tox 30c, Sabadilla 30c, Sambucus nig 4x, Silicea 6c, 30c, 200c, Sinusitisinum 30c, 200c, Spigelia anth 6c, Sulphur 6c, Symphytum 6x, Teucruim mar 6c, Thuja 30c.

Inactive Ingredients

USP Alcohol, Glycerin, Purified Water

Indications

A natural homeopathic medicine that may provide support for a healthy nasal and sinus tract. May aid with a runny nose, watery eyes, sneezing and congestion. Claims based on traditional homeopathic practice and principles not based on modern medical theory or practice.

PACKAGE LABEL

Add image transcription here...

Add image transcription here...